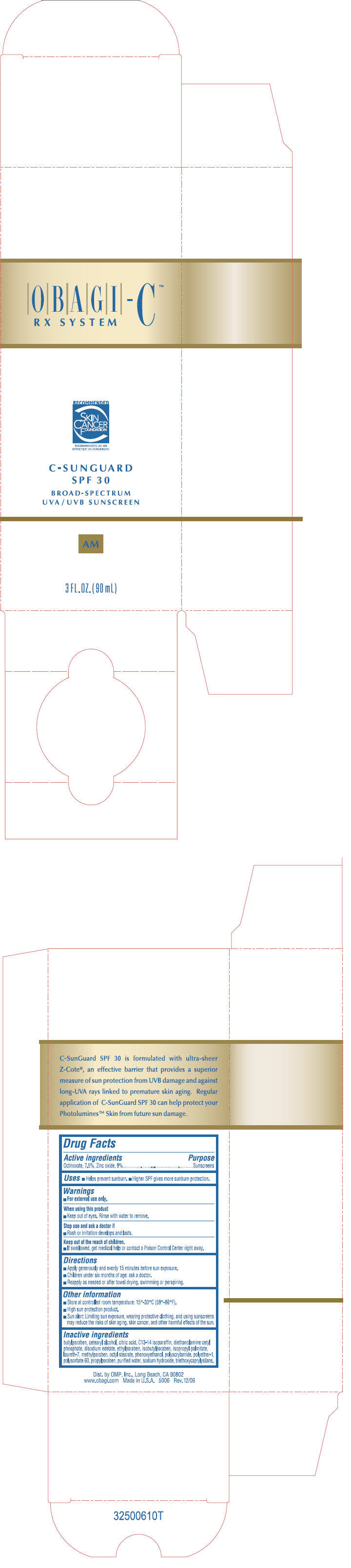 DRUG LABEL: Obagi-C Rx System C-Sunguard
NDC: 62032-107 | Form: CREAM
Manufacturer: OMP, Inc.
Category: otc | Type: HUMAN OTC DRUG LABEL
Date: 20190917

ACTIVE INGREDIENTS: OCTINOXATE 75 mg/1 mL; ZINC OXIDE 90 mg/1 mL
INACTIVE INGREDIENTS: ISOPROPYL PALMITATE; WATER; ETHYLHEXYL STEARATE; CETOSTEARYL ALCOHOL; POLYSORBATE 60; C13-14 ISOPARAFFIN; METHYLPARABEN; LAURETH-7; PROPYLPARABEN; EDETATE DISODIUM; BUTYLPARABEN; DIETHANOLAMINE CETYL PHOSPHATE; PHENOXYETHANOL; ETHYLPARABEN; ISOBUTYLPARABEN; SODIUM HYDROXIDE; TRIETHOXYCAPRYLYLSILANE; CITRIC ACID MONOHYDRATE

OBAGI-C™
RX SYSTEM

Drug Facts

Active ingredients

Octinoxate, 7.5%, Zinc oxide, 9%

Purpose

Sunscreens

Uses

- Helps prevent sunburn.
- Higher SPF gives more sunburn protection.

Warnings

- For external use only.

When using this product

- Keep out of eyes. Rinse with water to remove.

Stop use and ask a doctor if

- Rash or irritation develops and lasts.

Keep out of the reach of children

If swallowed, get medical help or contact a Poison Control Center right away.

Directions

- Apply generously and evenly 15 minutes before sun exposure.
- Children under six months of age: ask a doctor.
- Reapply as needed or after towel drying, swimming or perspiring.

Other information

- Store at controlled room temperature: 15°-30°C (59°-86°F).
- High sun protection product.
- Sun alert: Limiting sun exposure, wearing protective clothing, and using sunscreens may reduce the risks of skin aging, skin cancer, and other harmful effects of the sun.

Inactive ingredients

butylparaben, cetearyl alcohol, citric acid, C13-14 isoparaffin, diethanolamine cetyl phosphate, disodium edetate, ethylparaben, isobutylparaben, isopropyl palmitate, laureth-7, methylparaben, octyl stearate, phenoxyethanol, polyacrylamide, polyether-1, polysorbate 60, propylparaben, purified water, sodium hydroxide, triethoxycaprylysilane.

Dist. by OMP, Inc. Long Beach, CA 90802

PRINCIPAL DISPLAY PANEL - 90 mL Bottle Carton

OBAGI-C™
RX SYSTEM

RECOMMENDED
SKIN
CANCER
FOUNDATION
RECOMMENDED AS AN
EFFECTIVE UV SUNSCREEN

C-SUNGUARD
SPF 30

BROAD-SPECTRUM
UVA / UVB SUNSCREEN

AM

3 FL. OZ. (90 mL)